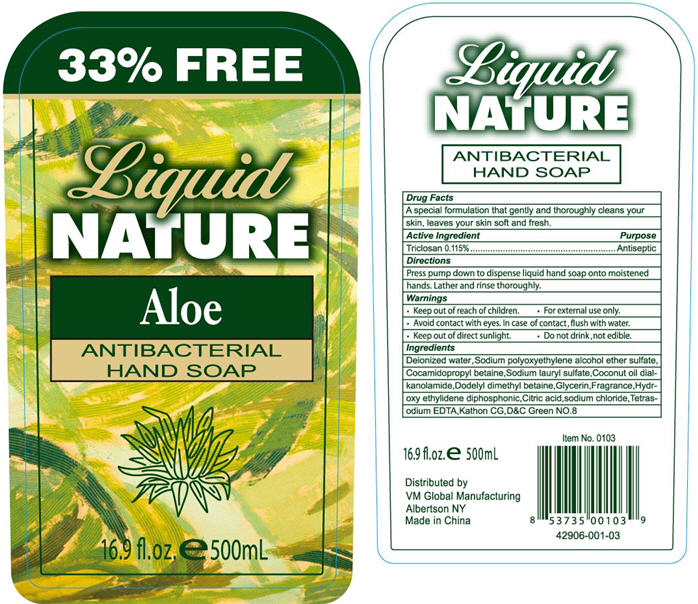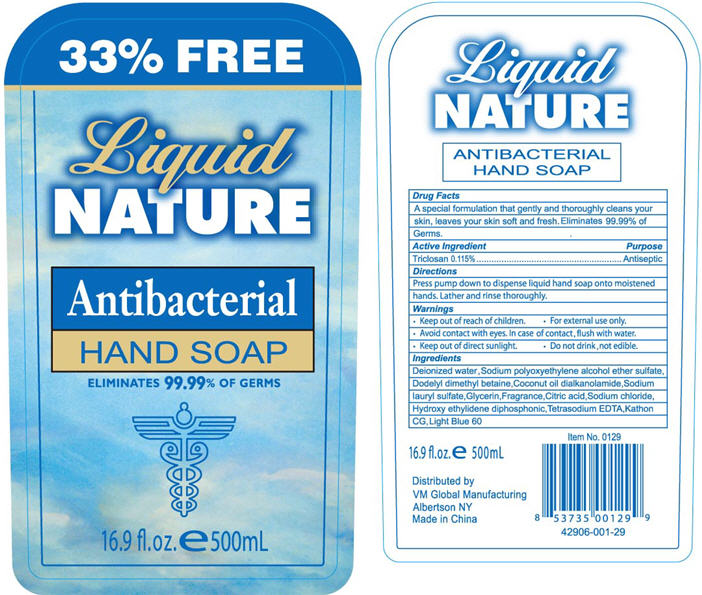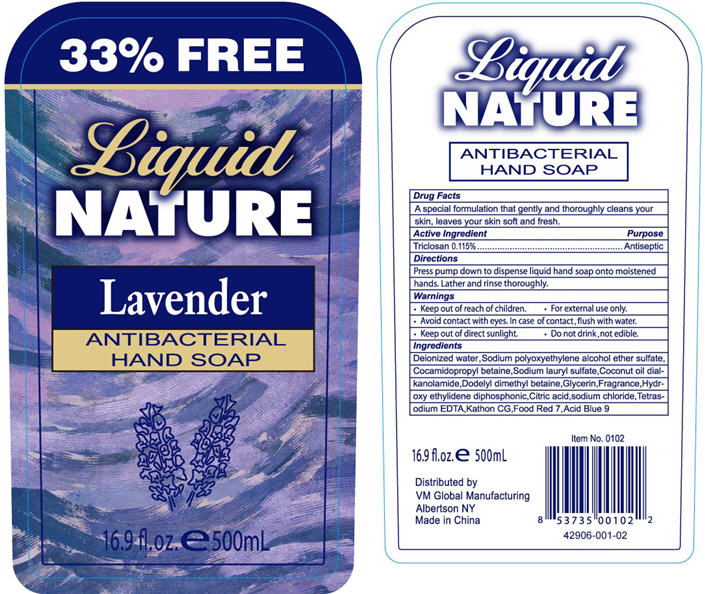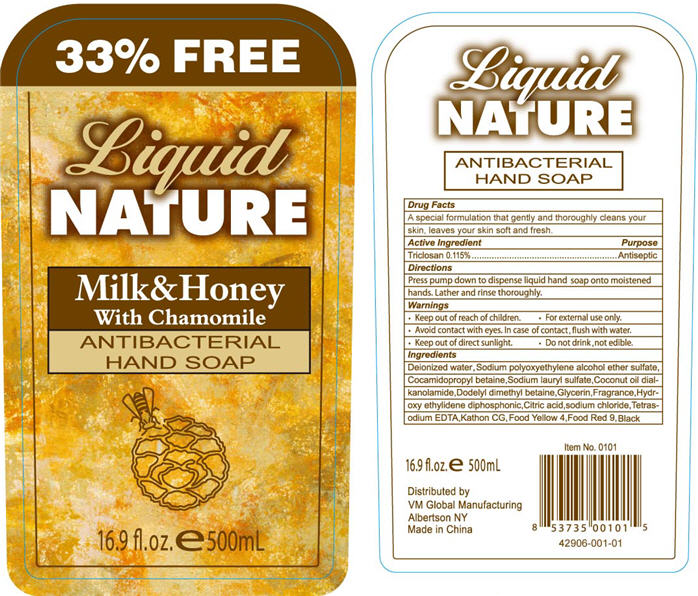 DRUG LABEL: Liquid Nature Antibacterial Hand Soap
NDC: 42906-001 | Form: SOLUTION
Manufacturer: VM Global Manufacturers Group Inc.
Category: otc | Type: HUMAN OTC DRUG LABEL
Date: 20091112

ACTIVE INGREDIENTS: TRICLOSAN 0.575 mL/500 mL

Liquid Nature Hand Soap - Aloe, Antibacterial, Lavender, Milk and Honey

USES

Aloe, Lavender, Milk and Honey

A special formulation that gently and thoroughly cleans your skin, leaves your skin soft and fresh.

Antibacterial

A special formulation that gently and thoroughly cleans your skin, leaves your skin soft and fresh. Eliminates 99.99% of Germs.

ACTIVE INGREDIENTS

Triclosan

PURPOSE

Antiseptic

DIRECTIONS

Press pump down to dispense liquid hand soap onto moistened hands. Lather and rinse thoroughly.

WARNINGS

- Keep out of reach of children.
- For external use only.
- Avoid contact with eyes. In case of contact, flush with water.
- Keep out of direct sunlight.
- Do not drink, not edible.

INACTIVE INGREDIENTS

Aloe

Deionized water, Sodium polyoxyethylene alcohol ether sulfate, Cocamidopropyl betaine, Sodium lauryl sulfate, Coconut oil dialkanolamide, Dodelyl dimethyl betaine, Glycerin, Fragrance, Hydroxy ethylidene diphosphonic, Citric acid, Sodium chloride, Tetrasodium EDTA, Kathon CG, D&C Green NO.8

Antibacterial

Deionized water, Sodium polyoxyethylene alcohol ether sulfate, Dodelyl dimethyl betaine, Coconut oil dialkanolamide, Sodium lauryl sulfate, Glycerin, Fragrance, Citric acid, Sodium chloride, Hydroxy ethylidene diphosphonic, Tetrasodium EDTA, Kathon CG, Light Blue 60

Lavender

Deionized water, Sodium polyoxyethylene alcohol ether sulfate, Cocamidopropyl betaine, Sodium lauryl sulfate, Coconut oil dialkanolamide, Dodelyl dimethyl betaine, Glycerin, Fragrance, Hydroxy ethylidene diphosphonic, Citric acid, Sodium chloride, Tetrasodium EDTA, Kathon CG, Food Red 7, Acid Blue 9

Milk and Honey

Deionized water, Sodium polyoxyethylene alcohol ether sulfate, Cocamidopropyl betaine, Sodium lauryl sulfate, Coconut oil dialkanolamide, Dodelyl dimethyl betaine, Glycerin, Fragrance, Hydroxy ethylidene diphosphonic, Citric acid, Sodium chloride, Tetrasodium EDTA, Kathon CG, Food Yellow 4, Food Red 9, Black

PRINCIPAL DISPLAY PANEL - ALOE

Liquid
NATURE
Aloe
ANTIBACTERIAL HAND SOAP

16.9 fl.oz. ℮ 500mL

Distributed by
VM Global Manufacturing
Albertson, NY
Made in China

PRINCIPAL DISPLAY PANEL - ANTIBACTERIAL

Liquid
NATURE
Antibacterial
HAND SOAP
ELIMINATES 99.99% OF GERMS

16.9 fl.oz. ℮ 500mL

Distributed by
VM Global Manufacturing
Albertson, NY
Made in China

PRINCIPAL DISPLAY PANEL - LAVENDER

Liquid
NATURE
Lavender
ANTIBACTERIAL HAND SOAP

16.9 fl.oz. ℮ 500mL

Distributed by
VM Global Manufacturing
Albertson, NY
Made in China

PRINCIPAL DISPLAY PANEL - MILK AND HONEY

Liquid
NATURE
Milk&Honey
With Chamomile
ANTIBACTERIAL HAND SOAP

16.9 fl.oz. ℮ 500mL

Distributed by
VM Global Manufacturing
Albertson, NY
Made in China